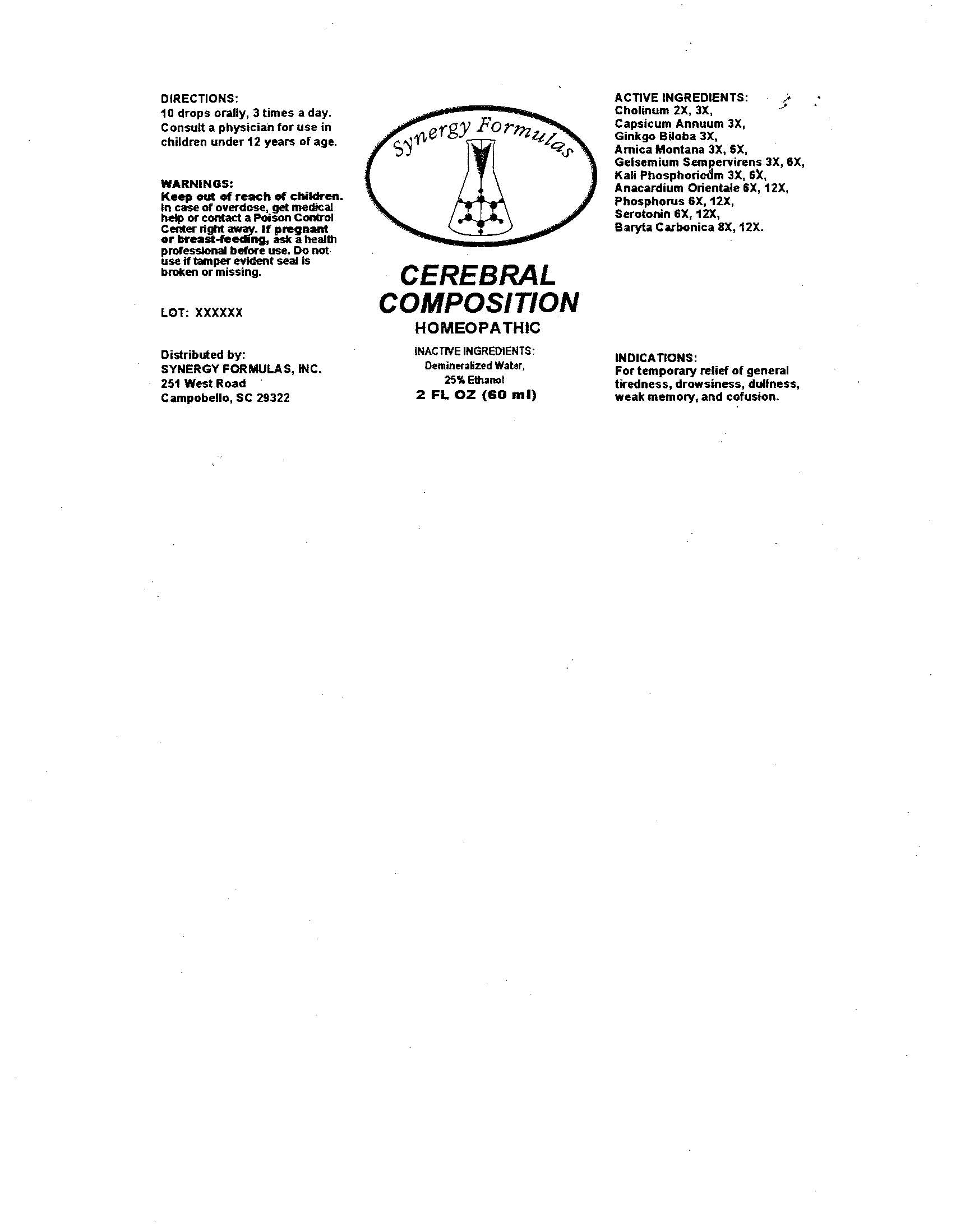 DRUG LABEL: Cerebral Composition
NDC: 57520-0321 | Form: LIQUID
Manufacturer: Apotheca Company
Category: homeopathic | Type: HUMAN OTC DRUG LABEL
Date: 20100701

ACTIVE INGREDIENTS: CHOLINE HYDROXIDE 3 [hp_X]/1 mL; CHILI PEPPER 3 [hp_X]/1 mL; GINKGO 3 [hp_X]/1 mL; ARNICA MONTANA 6 [hp_X]/1 mL; GELSEMIUM SEMPERVIRENS ROOT 6 [hp_X]/1 mL; POTASSIUM PHOSPHATE, DIBASIC 6 [hp_X]/1 mL; SEMECARPUS ANACARDIUM JUICE 12 [hp_X]/1 mL; BARIUM CARBONATE 12 [hp_X]/1 mL; PHOSPHORUS 12 [hp_X]/1 mL; SEROTONIN 12 [hp_X]/1 mL
INACTIVE INGREDIENTS: WATER; ALCOHOL

Cerebral Composition

ACTIVE INGREDIENT

ACTIVE INGREDIENTS: Cholinum 2X, 3X, Capsicum annuum 3X, Ginkgo biloba 3X, Arnica montana 3X, 6X, Gelsemium sempervirens 3X, 6X, Kali phosphoricum 3X, 6X, Anacardium orientale 6X, 12X, Baryta carbonica 6X, 12X, Phosphorus 6X, 12X, Serotonin 6X, 12X.

PURPOSE

INDICATIONS: For temporary relief of general tiredness, drowsiness, dullness, weak memory, and confusion.

WARNINGS

WARNINGS: Keep out of reach of children. In case of overdose, get medical help or contact a Poison Control Center right away.

If pregnant or breast-feeding, ask a health professional before use.

Do not use if tamper evident seal is broken or missing.

DOSAGE AND ADMINISTRATION

DIRECTIONS: 10 drops orally, 3 times a day. Consult a physician for use in children under 12 years of age.

INACTIVE INGREDIENTS: Demineralized water, 25% Ethanol

PACKAGE LABEL

SYNERGY FORMULAS

CEREBRAL COMPOSITION

HOMEOPATHIC

2 FL OZ (60 ML)